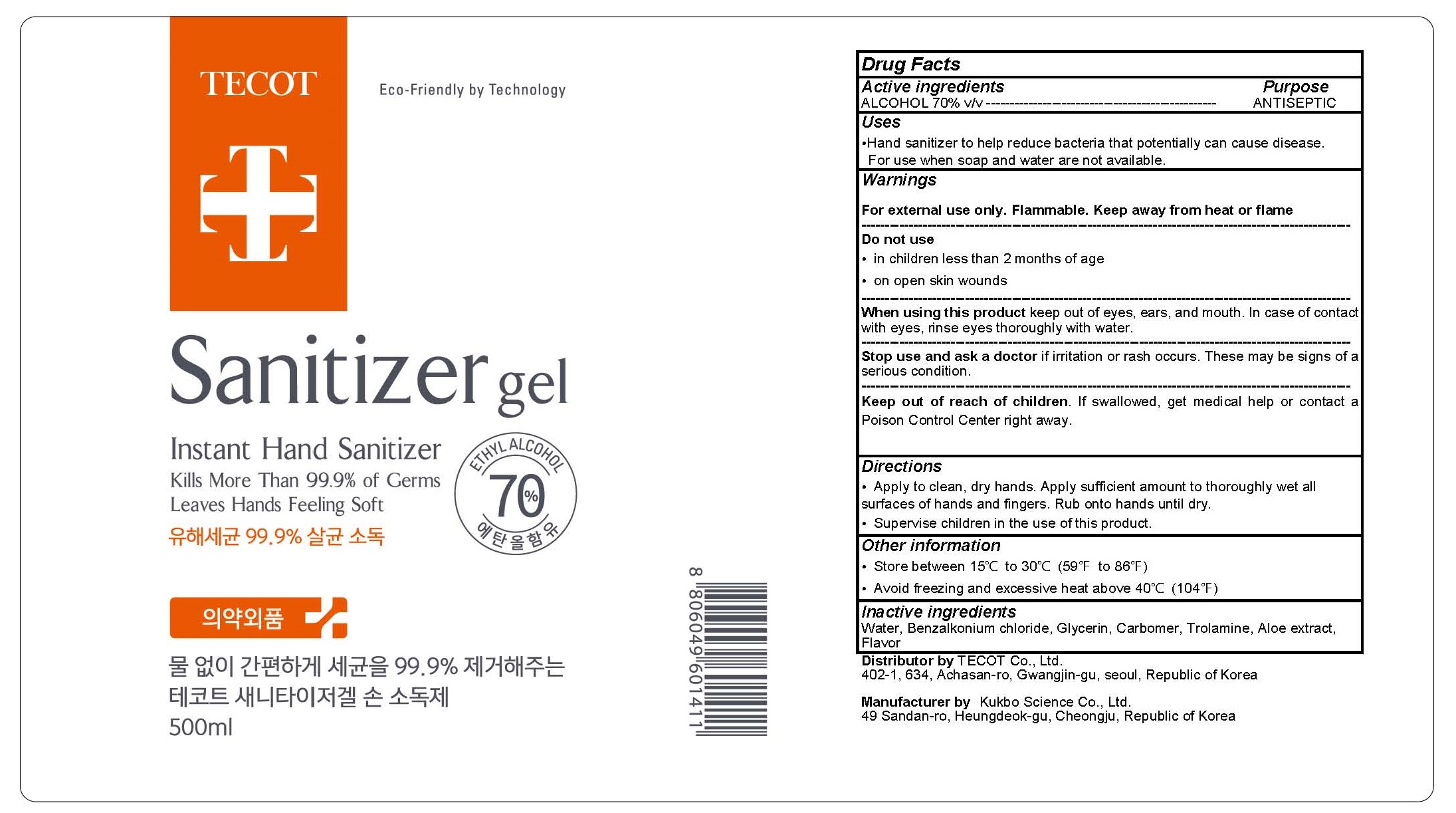 DRUG LABEL: TECOT SANITIZER
NDC: 78452-010 | Form: GEL
Manufacturer: TECOT Co.,Ltd.
Category: otc | Type: HUMAN OTC DRUG LABEL
Date: 20200602

ACTIVE INGREDIENTS: ALCOHOL 350 mL/500 mL
INACTIVE INGREDIENTS: Water; Benzalkonium chloride; Glycerin; CARBOMER HOMOPOLYMER, UNSPECIFIED TYPE; TROLAMINE; ALOE

ACTIVE INGREDIENT

ALCOHOL 70% v/v

INACTIVE INGREDIENTS

Water, Benzalkonium chloride, Glycerin, Carbomer, Trolamine, Aloe extract, Flavor

PURPOSE

ANTISEPTIC

WARNINGS

For external use only. Flammable. Keep away from heat or flame
--------------------------------------------------------------------------------------------------------
Do not use
• in children less than 2 months of age
• on open skin wounds
--------------------------------------------------------------------------------------------------------
When using this product keep out of eyes, ears, and mouth. In case of contact with eyes, rinse eyes thoroughly with water.
--------------------------------------------------------------------------------------------------------
Stop use and ask a doctor if irritation or rash occurs. These may be signs of a serious condition.

KEEP OUT OF REACH OF CHILDREN

If swallowed, get medical help or contact a Poison Control Center right away.

Uses

Hand sanitizer to help reduce bacteria that potentially can cause disease.
For use when soap and water are not available.

Directions

• Apply to clean, dry hands. Apply sufficient amount to thoroughly wet all surfaces of hands and fingers. Rub onto hands until dry.
• Supervise children in the use of this product.

Other information

• Store between 15℃ to 30℃ (59℉ to 86℉)
• Avoid freezing and excessive heat above 40℃ (104℉)